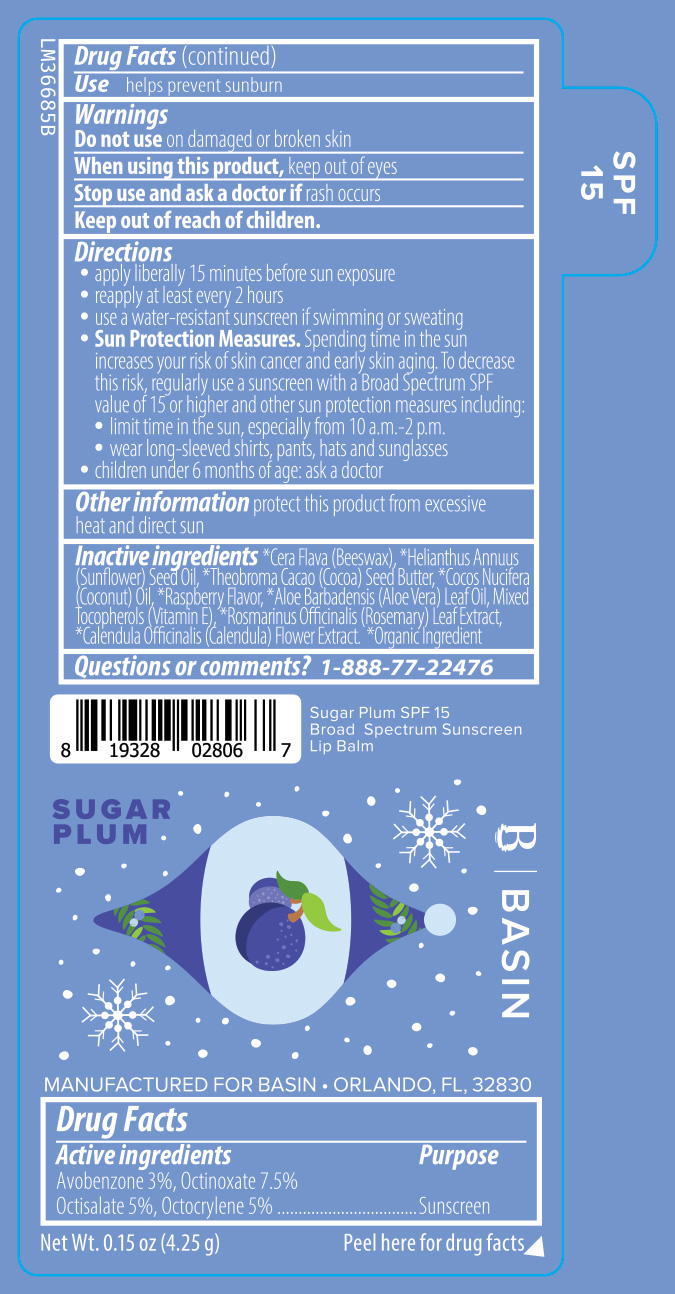 DRUG LABEL: Basin Sugar Plum SPF 15 Broad Spectrum Sunscreen Lip Balm
NDC: 84603-124 | Form: STICK
Manufacturer: Retail Concepts of Minnesota, Inc.
Category: otc | Type: HUMAN OTC DRUG LABEL
Date: 20250903

ACTIVE INGREDIENTS: OCTINOXATE 7.5 g/100 g; AVOBENZONE 3 g/100 g; OCTOCRYLENE 5 g/100 g; OCTISALATE 5 g/100 g
INACTIVE INGREDIENTS: ROSEMARY; COCOA BUTTER; ALOE VERA LEAF; TOCOPHEROL; CALENDULA OFFICINALIS FLOWER; SUNFLOWER OIL; YELLOW WAX; COCONUT OIL

Basin Sugar Plum SPF 15 Broad Spectrum Sunscreen Lip Balm (124S Raspberry)

Active ingredients

Avobenzone 3%, Octinoxate 7.5%

Octisalate 5%, Octocrylene 5%

Purpose

Sunscreen

INDICATIONS AND USAGE

Usehelps prevent sunburn

WARNINGS

on damaged or broken skin

Do not use on damaged or broken skin

When using this product, keep out of eyes

Stop use and ask a doctor if rash occurs

Keep out of reach of children.

DOSAGE AND ADMINISTRATION

Direction

- apply liberally 15 minutes before sun exposure
- reapply at least every 2 hours
- use a water resistance sunscreen if swimming or sweating
- Sun Protection Measures Spending time in the sun increases your risk of skin cancer and early skin aging. To decrease this risk, regularly use a sunscreen with a Broad Spectrum SPF value of 15 or higher and other sun protection measures including:
- limit time in the sun, especially from 10 a.m.-2 p.m.
- wear long-sleeved shirts, pants, hats, and sunglasses
- children under 6 months of age: ask a doctor

STORAGE AND HANDLING

Other informationprotect this product from excessive heat and direct sun

INACTIVE INGREDIENT

Inactive ingredients*Cera Flava (Beeswax), *Helianthus Annuus (Sunflower) Seed Oil, *Theobroma Cacao (Cocoa) Seed Butter, *Cocos Nucifera (Coconut) Oil, *Raspberry Flavor, *Aloe Barbadensis (Aloe Vera) Leaf Oil, Mixed Tocopherols (Vitamin E), *Rosmarinus Officinalis (Rosemary) Leaf Extract, *Calendula Officinalis (Calendula) Flower Extract. *Organic Ingredient

Questions or comments?1-888-77-22476

Sugar Plum SPF 15

Broad Spectrum Sunscreen

Lip Balm

SUGAR PLUM

B | BASIN

MANUFACTURED FOR BASIN - ORLANDO, FL. 32830

Net Wt. 0.15 oz (4.25 g) Peel here for drug facts

SPF

15

PACKAGE LABEL

Net Wt. 0.15 oz (4.25 g)